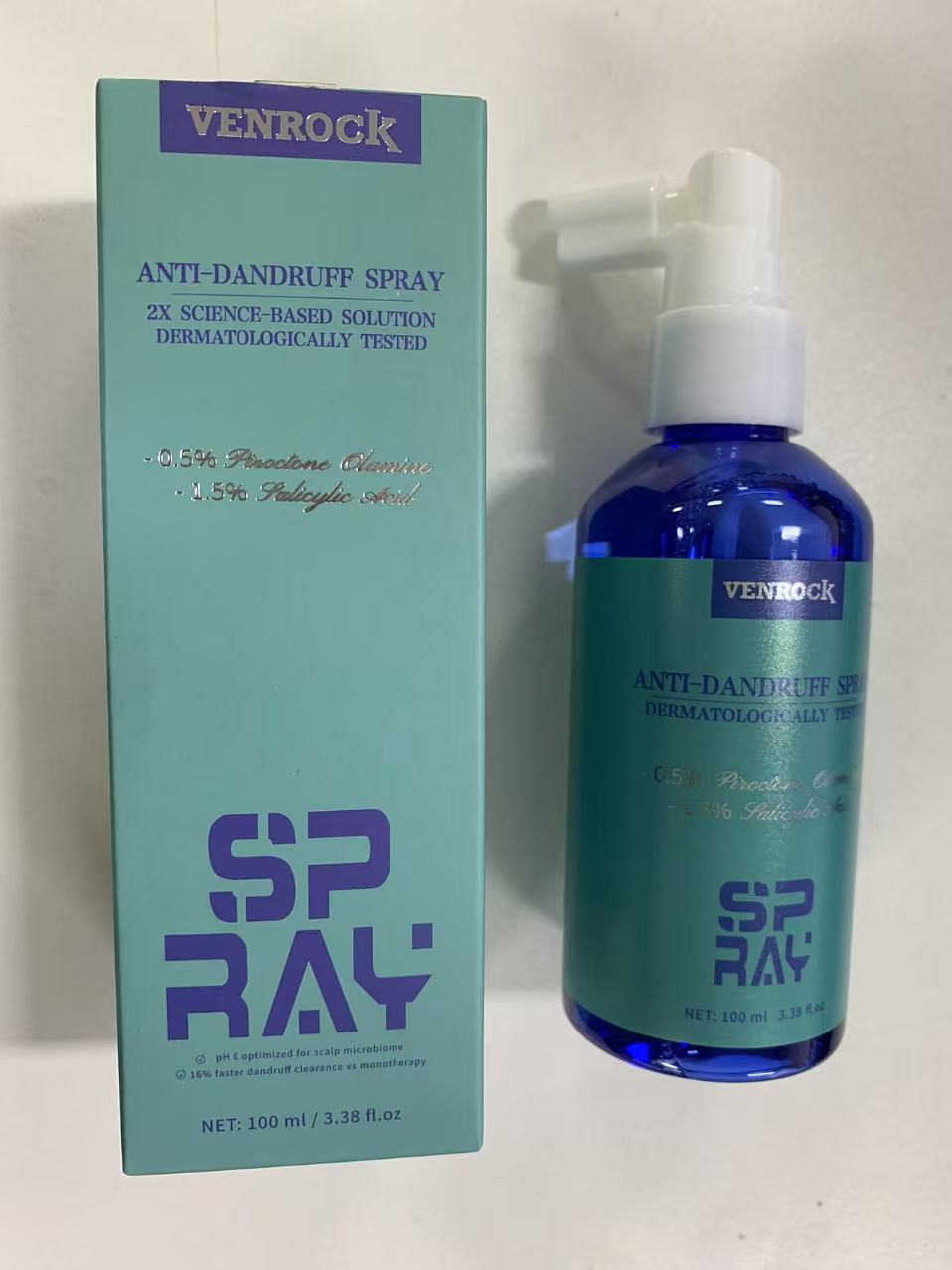 DRUG LABEL: VENROCK
NDC: 85772-0002 | Form: SPRAY
Manufacturer: Guangzhou Oupeng Cosmetics Co., Ltd.
Category: otc | Type: HUMAN OTC DRUG LABEL
Date: 20250612

ACTIVE INGREDIENTS: PIROCTONE OLAMINE 0.5 g/100 g; SALICYLIC ACID 1.5 g/100 g
INACTIVE INGREDIENTS: PHENOXYETHANOL 0.5 g/100 g; POLYOXYL 40 HYDROGENATED CASTOR OIL 1.2 g/100 g; ALCOHOL 3 g/100 g; BUTYLENE GLYCOL 0.3 g/100 g; SWERTIA CHIRAYITA LEAF 0.25 g/100 g; GENTIANA MACROPHYLLA ROOT 0.25 g/100 g; AQUA 86.5 g/100 g; GLYCERETH-25 PCA ISOSTEARATE 1.2 g/100 g; MENTHOL 0.5 g/100 g; BENZOIC ACID 0.3 g/100 g; GENTIANA SCABRA ROOT 0.25 g/100 g; PROPYLENE GLYCOL 2.5 g/100 g; COCAMIDOPROPYL PG-DIMONIUM CHLORIDE PHOSPHATE 0.45 g/100 g; CINNAMOMUM CAMPHORA (CAMPHOR) LEAF OIL 0.8 g/100 g

Active ingredient(s)

1. Piroctone Olamine 0.5%
2. Salicylic Acid 1.5%

Purpose(s)

1. Anti-dandruff (dissolves oil plugs and unclogs pores)
2. Anti-dandruff (inhibits Malassezia)

Uses

- Helps prevent and control recurrence of the symptoms of dandruff
- Helps prevent recurrence of the flaking and itching associated with dandruff

Warnings

For external use only.

Do not use

- On scalp that is broken or inflamed
- On children under 12 years of age
- If you are pregnant

When using this product

- Avoid contact with eyes. If contact occurs, rinse eyes thoroughly with water
- Avoid contact with mucous membranes.

Stop use and ask a doctor if

- Condition worsens or does not improve after regular use
- Allergic reaction occurs or irritation persists

PREGNANCY OR BREAST FEEDING SECTION

If pregnant or breast-feeding, ask a health professional before use

Keep out of reach of children

In case of accidental ingestion, get medical help or contact a Poison Control Center right away

Directions

- Shake well before use
- Apply to affected areas one to four times daily or as directed by a doctor
- For best results, use at least twice a week or as directed by a doctor
- Application: Hold 15-20 cm (4-6 inches) from dry scalp and spray onto affected areas. Use fingertips to massage into scalp for 1-2 minutes until fully absorbed. Do not rinse.

Other information

Store in a cool, dry place away from direct sunlight

Inactive ingredients

AQUA, ALCOHOL, PROPYLENE GLYCOL, SALICYLIC ACID, PEG-40 HYDROGENATED CASTOR OIL, GLYCERETH-25 PCA ISOSTEARATE, CINNAMOMUM CAMPHORA (CAMPHOR) LEAF OIL, PHENOXYETHANOL, MENTHOL, COCAMIDOPROPYL PG-DIMONIUM CHLORIDE PHOSPHATE, PIROCTONE OLAMINE, BENZOIC ACID, BUTYLENE GLYCOL, SWERTIA CHIRATA EXTRACT, GENTIANA MACROPHYLLA ROOT EXTRACT, GENTIANA SCABRA EXTRACT

Questions or comments?

934-935-7135 / Yiqinzhi726@gmail.com

Box Front Panel

VENROCK

ANTI-DANDRUFF SPRAY

2X SCIENCE-BASED SOLUTION
DERMATOLOGICALLY TESTED

- 0.5% Piroctone Olamine
- 1.5% Salicylic Acid

SPRAY

√ pH 6 optimized for scalp microbiome
√ 16% faster dandruff clearance vs monotherapy

NET: 100 ml / 3.38 fl.oz